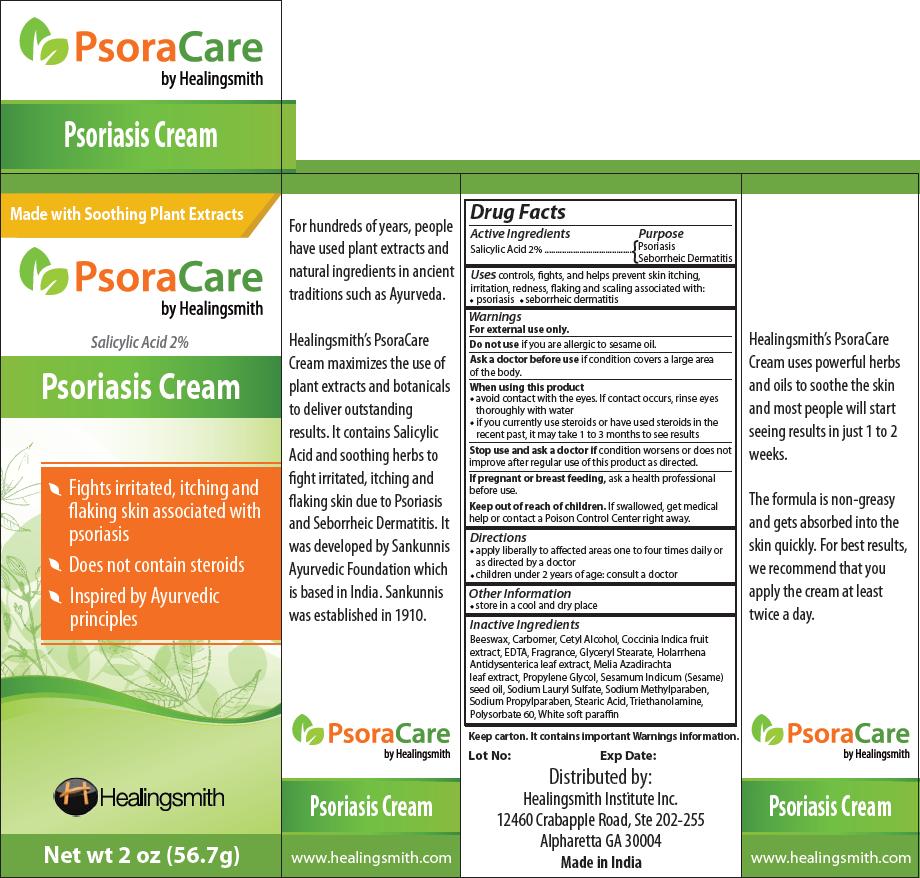 DRUG LABEL: PsoraCare
NDC: 76066-002 | Form: CREAM
Manufacturer: Healingsmith Institute Inc.
Category: otc | Type: HUMAN OTC DRUG LABEL
Date: 20111128

ACTIVE INGREDIENTS: SALICYLIC ACID 1.1 g/56.7 g
INACTIVE INGREDIENTS: YELLOW WAX; COCCINIA GRANDIS FRUIT; EDETIC ACID; HOLARRHENA PUBESCENS BARK; AZADIRACHTA INDICA LEAF; PROPYLENE GLYCOL; SESAME OIL; SODIUM LAURYL SULFATE; METHYLPARABEN SODIUM; PROPYLPARABEN SODIUM; STEARIC ACID; TROLAMINE; POLYSORBATE 60; PARAFFIN

ACTIVE INGREDIENT

Salicylic Acid 2%

PURPOSE

Psoriasis, Seborrheic Dermatitis

INDICATIONS AND USAGE

controls, fights, and helps prevent skin itching, irritation, redness, flaking and scaling associated with:

- psoriasis
- seborrheic dermatitis

WARNINGS

For external use only.

Do not use if you are allergic to sesame oil.

Ask a doctor before use if condition covers a large area of the body.

When using this product

- avoid contact with the eyes. If contact occurs, rinse eyes thoroughly with water
- if you currently use steroids or have used steroids in the recent past, it may take 1 to 3 months to see results

Stop use and ask a doctor if condition worsens or does not improve after regular use of this product as directed.

PREGNANCY OR BREAST FEEDING

If pregnant or breast feeding, ask a health professional before use.

Keep out of reach of children. If swallowed, get medical help or contact a Poison Control Center right away.

DOSAGE AND ADMINISTRATION

- apply liberally to affected areas one to four times daily or as directed by a doctor
- children under 2 years of age: consult a doctor

STORAGE AND HANDLING

store in a cool and dry place

INACTIVE INGREDIENT

Beeswax, Carbomer, Cetyl Alcohol, Coccinia Indica fruit extract, EDTA, Fragrance, Glyceryl Stearate, Holarrhena Antidysenterica leaf extract, Melia Azadirachta leaf extract, Propylene Glycol, Sesamum Indicum (Sesame) seed oil, Sodium Lauryl Sulfate, Sodium Methylparaben, Sodium Propylparaben, Stearic Acid, Triethanolamine, Polysorbate 60, White soft paraffin